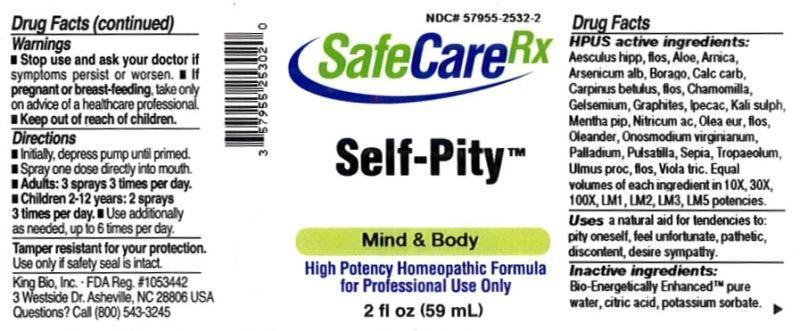 DRUG LABEL: Self Pity
NDC: 57955-2532 | Form: LIQUID
Manufacturer: King Bio Inc.
Category: homeopathic | Type: HUMAN OTC DRUG LABEL
Date: 20150810

ACTIVE INGREDIENTS: AESCULUS HIPPOCASTANUM FLOWER 10 [hp_X]/59 mL; ALOE 10 [hp_X]/59 mL; ARNICA MONTANA 10 [hp_X]/59 mL; ARSENIC TRIOXIDE 10 [hp_X]/59 mL; BORAGE 10 [hp_X]/59 mL; OYSTER SHELL CALCIUM CARBONATE, CRUDE 10 [hp_X]/59 mL; CARPINUS BETULUS FLOWERING TOP 10 [hp_X]/59 mL; MATRICARIA RECUTITA 10 [hp_X]/59 mL; GELSEMIUM SEMPERVIRENS ROOT 10 [hp_X]/59 mL; GRAPHITE 10 [hp_X]/59 mL; IPECAC 10 [hp_X]/59 mL; POTASSIUM SULFATE 10 [hp_X]/59 mL; MENTHA PIPERITA 10 [hp_X]/59 mL; NITRIC ACID 10 [hp_X]/59 mL; OLEA EUROPAEA FLOWER 10 [hp_X]/59 mL; NERIUM OLEANDER LEAF 10 [hp_X]/59 mL; ONOSMODIUM VIRGINIANUM WHOLE 10 [hp_X]/59 mL; PALLADIUM 10 [hp_X]/59 mL; PULSATILLA VULGARIS 10 [hp_X]/59 mL; SEPIA OFFICINALIS JUICE 10 [hp_X]/59 mL; TROPAEOLUM MAJUS 10 [hp_X]/59 mL; ULMUS PROCERA FLOWERING TWIG 10 [hp_X]/59 mL; VIOLA TRICOLOR 10 [hp_X]/59 mL
INACTIVE INGREDIENTS: WATER; CITRIC ACID MONOHYDRATE; POTASSIUM SORBATE

Self Pity

ACTIVE INGREDIENT

Drug Facts__________________________________________________________________________________________________________

HPUS active ingredients: Aesculus hippocastanum, flos, Aloe socotrina, Arnica montana, Arsenicum album, Borago officinalis, Calcarea carbonica, Carpinus betulus, flos, Chamomilla, Gelsemium sempervirens, Graphites, Ipecacuanha, Kali sulphuricum, Mentha piperita, Nitricum acidum, Olea europaea, flos, Oleander, Onosmodium virginianum, Palladium metallicum, Pulsatilla, Sepia, Tropaeolum majus, Ulmus procera, flos, Viola tricolor.

INDICATIONS AND USAGE

Uses a natural aid for tendencies to: pity oneself, feel unfortunate, pathetic, discontent, desire sympathy.

Inactive Ingredients:

Bio-Energetically Enhanced™ pure water, citric acid and potassium sorbate.

Warnings

- Stop use and ask your doctor if symptoms persist or worsen.
- If pregnant or breast-feeding, take only on advice of a healthcare professional.

- Keep out of reach of children.

Directions

- Initially, depress pump until primed.
- Spray one dose directly into mouth.
- Adults: 3 sprays 3 times per day.
- Children 2-12: 2 sprays 3 times per day.
- Use additionally as needed, up to 6 times per day.

OTHER SAFETY INFORMATION

Tamper resistant for your protection. Use only if seal is intact.

PURPOSE

Uses a natural aid for tendencies to:

- pity oneself
- feel unfortunate
- pathetic
- discontent
- desire sympathy